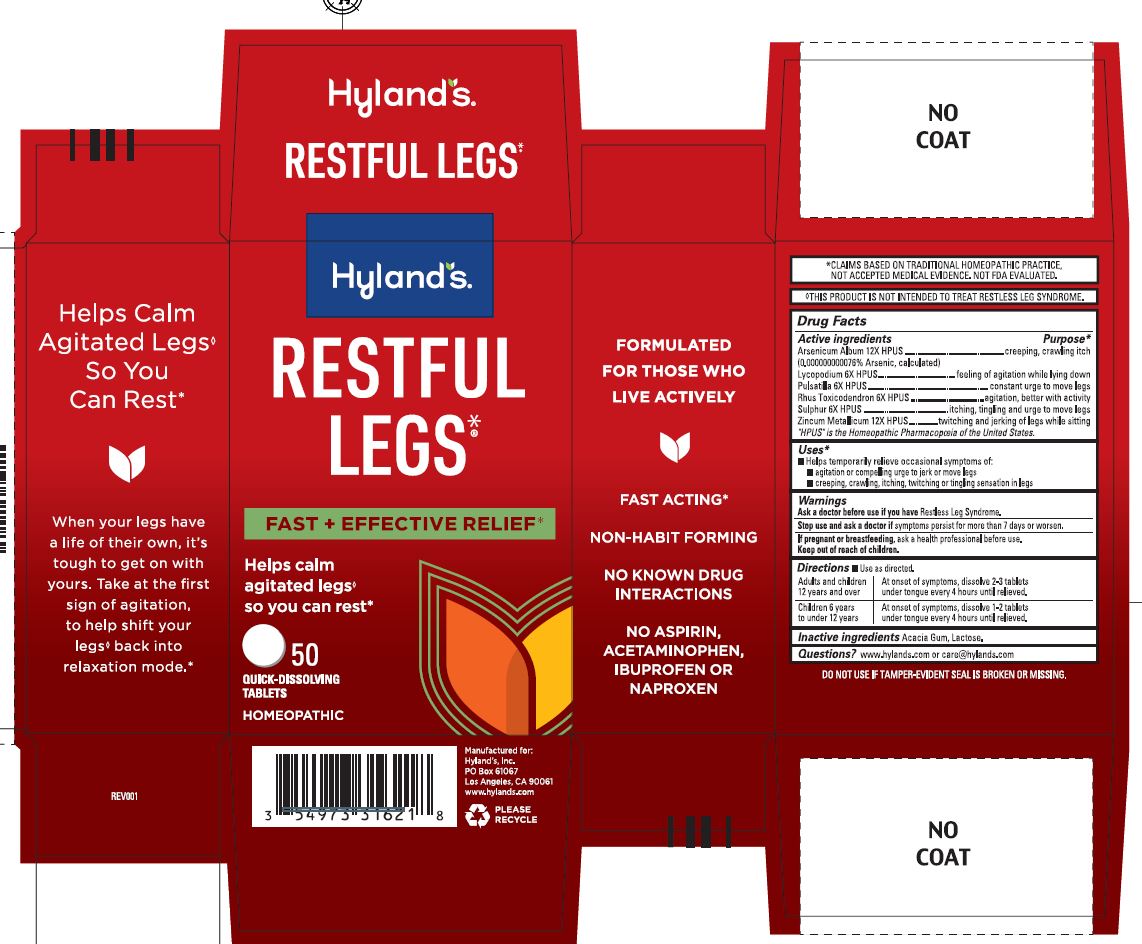 DRUG LABEL: Restful Legs
NDC: 54973-3162 | Form: TABLET, SOLUBLE
Manufacturer: Hyland's Inc.
Category: homeopathic | Type: HUMAN OTC DRUG LABEL
Date: 20250206

ACTIVE INGREDIENTS: ARSENIC TRIOXIDE 12 [hp_X]/1 1; LYCOPODIUM CLAVATUM SPORE 6 [hp_X]/1 1; PULSATILLA VULGARIS 6 [hp_X]/1 1; TOXICODENDRON PUBESCENS LEAF 6 [hp_X]/1 1; SULFUR 6 [hp_X]/1 1; ZINC 12 [hp_X]/1 1
INACTIVE INGREDIENTS: LACTOSE

Restful Legs

PURPOSE

Temporarily relieves occasional symptoms of: agitation or compelling urge to jerk or move legs, creeping, crawling, itching, twitching or tingling sensation in legs.

Drug Facts

Active ingredients

Active ingredients | Purpose
Arsenicum Album 12X HPUS; (0.000000000076% Arsenic, calculated) | creeping, crawling itch
Lycopodium 6X HPUS | feeling of agitation while lying down
Pulsatilla 6X HPUS | constant urge to move legs
Rhus Toxicodendron 6X HPUS | agitation, better with activity
Sulphur 6X HPUS | itching, tingling and urge to move legs
Zincum Metallicum 12X HPUS | twitching and jerking of legs while sitting

"HPUS" is the Homeopathic Pharmacopoeia of the United States.

Uses

■ Helps temporarily relieves occasional symptoms of:

■ agitation or compelling urge to jerk or move legs

■ itching, tingling, or crawling sensations in the legs

Directions

■ Use as directed.

Adults and children 12 years and over | At onset of symptoms, dissolve 2-3 tablets under tongue every 4 hours until relieved.
Children 6 years to under 12 years | At onset of symptoms, dissolve 1-2 tablets under tongue every 4 hours until relieved.

Warnings

Ask a doctor before use if you have

Restless Leg Syndrome.

Stop use and ask a doctor if

symptoms persist for more than 7 days or worsen.

If pregnant or breastfeeding

Ask a health professional before use.

Inactive Ingredients

Acacia Gum, Lactose.

Questions?

www.hylands.com or care@hylands.com

Dosage and Administration

added bullets

Indications and Usage

Uses

Helps temporarily relieve occasional symptoms of:
agitation or compelling urge to jerk or move legs
creeping, crawling, itching, twitching or tingling sensation in legs

PRINCIPAL DISPLAY PANEL- Restful Legs 50 Count

Hyland's

NATURALS™

RESTFUL

LEGS

FAST + EFFECTIVE RELIEF*

Calms agitated

legs so you

can rest**

50

QUICK-DISSOLVING

TABLETS

HOMEOPATHIC